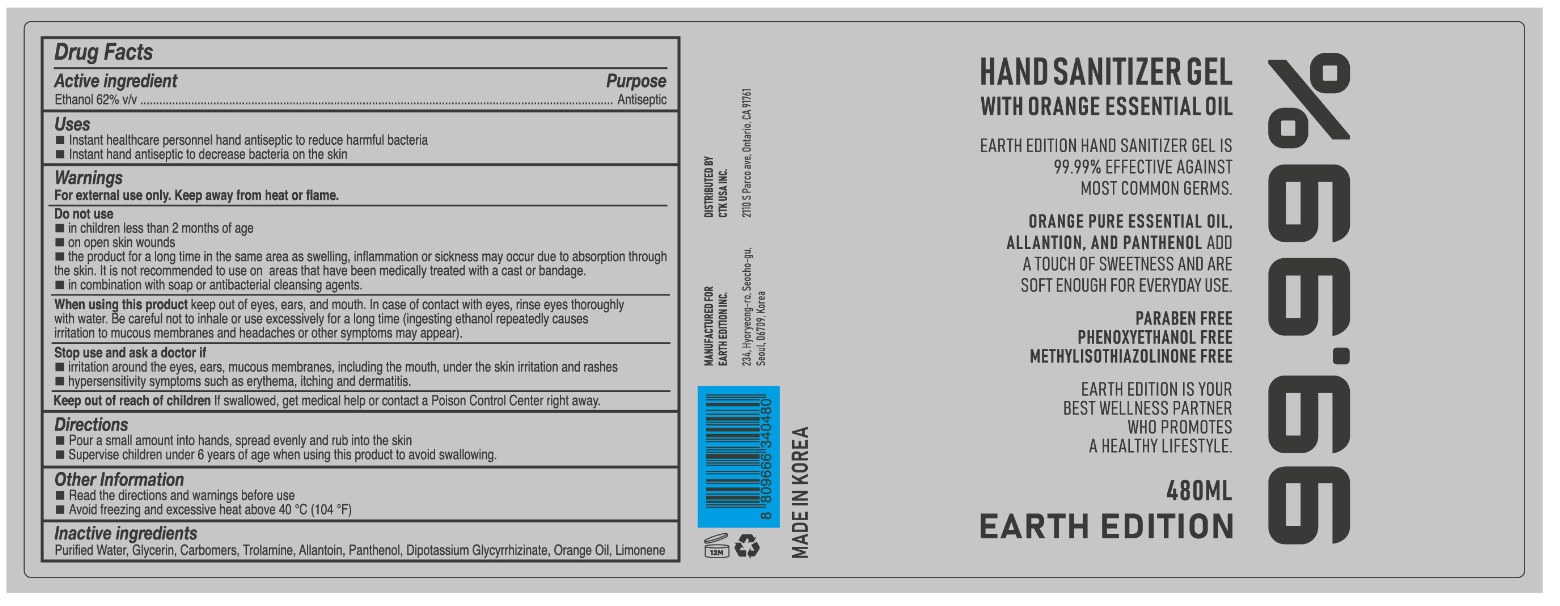 DRUG LABEL: EARTH EDITION HAND SANITIZER Gel
NDC: 76841-4806 | Form: GEL
Manufacturer: Earth Edition Inc.
Category: otc | Type: HUMAN OTC DRUG LABEL
Date: 20200510

ACTIVE INGREDIENTS: ALCOHOL 350 mL/500 mL
INACTIVE INGREDIENTS: GLYCYRRHIZINATE DIPOTASSIUM; GLYCERIN; ALLANTOIN; ORANGE OIL; CARBOMER HOMOPOLYMER, UNSPECIFIED TYPE; WATER; TROLAMINE; PANTHENOL; LIMONENE, (+)-

EARTH EDITION HAND SANITIZER Gel
480 mL
76841-4806-1